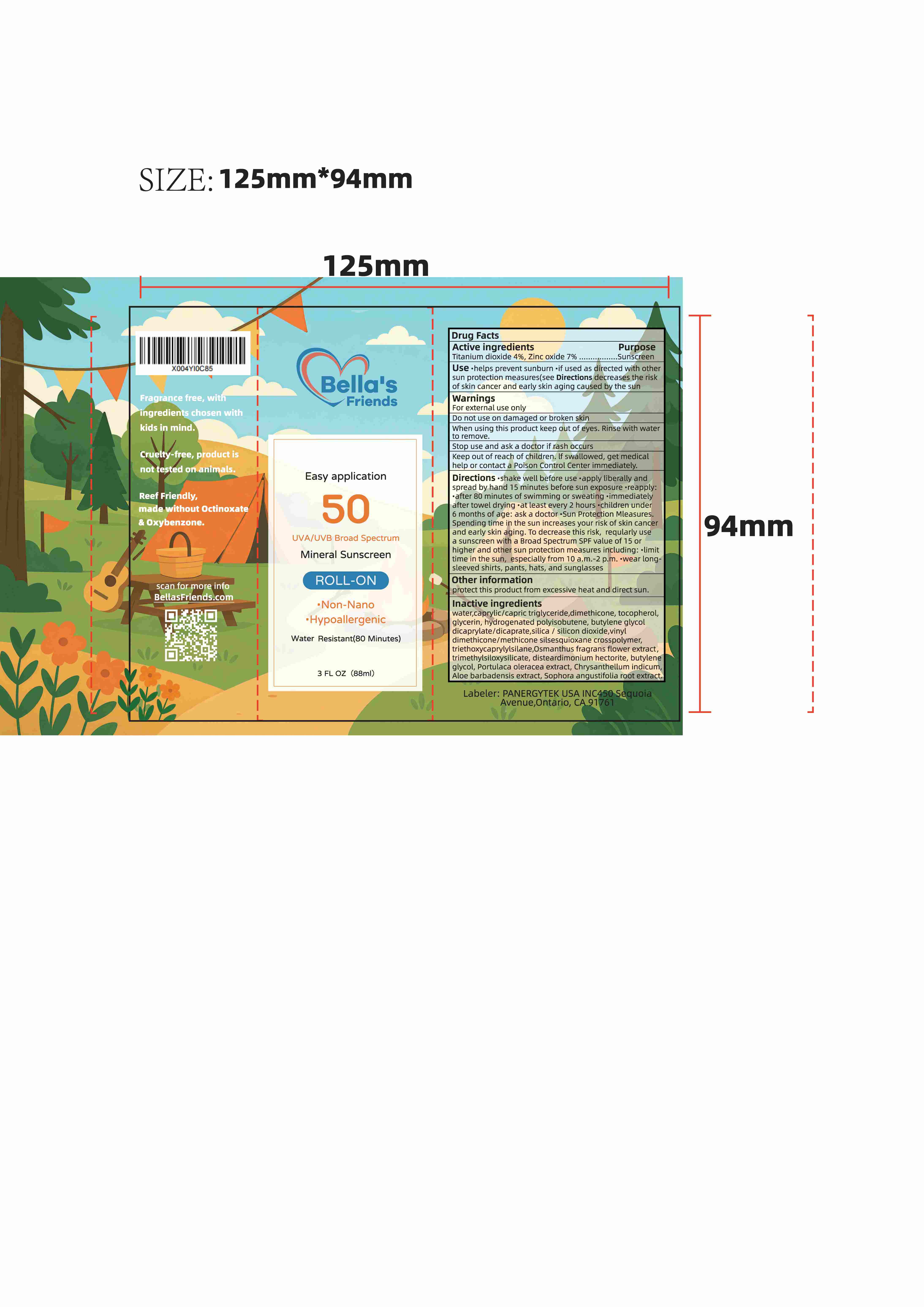 DRUG LABEL: Bellas Friends Roll-on Sunscreen
NDC: 85950-004 | Form: LOTION
Manufacturer: PANERGYTEK USA INC
Category: otc | Type: HUMAN OTC DRUG LABEL
Date: 20260104

ACTIVE INGREDIENTS: ZINC OXIDE 7 g/100 mL; TITANIUM DIOXIDE 4 g/100 mL
INACTIVE INGREDIENTS: PURSLANE; WATER; BUTYLENE GLYCOL; VINYL DIMETHICONE/METHICONE SILSESQUIOXANE CROSSPOLYMER; CHRYSANTHELLUM INDICUM FLOWER OIL; CAPRYLIC/CAPRIC/SUCCINIC TRIGLYCERIDE; DISTEARDIMONIUM HECTORITE; TOCOPHEROL; ALOE BARBADENSIS LEAF; TRIETHOXYCAPRYLYLSILANE; OSMANTHUS FRAGRANS FLOWER; HYDROGENATED POLYISOBUTENE 8; DIMETHICONE; BUTYLENE GLYCOL DICAPRYLATE/DICAPRATE; SILICON DIOXIDE; GLYCERIN; TRIMETHYLSILOXYSILICATE (M/Q 0.6-0.8); SOPHORA FLAVESCENS ROOT

85950-004 Bellas Friends Roll-on Sunscreen

Active ingredients
Purpose
Titanium dioxide 4%,Zinc oxide 7% ................Sunscreen

PURPOSE

USe.helps prevent sunburn .if used as directed with othersun protection measures(see Directions decreases the risk of skin cancer and early skin aging caused by the sun

Keep out of reach of children. If swallowed, get medical
help or contact a Poison Control Center immediately.

Warnings For external use only
Do not use on damaged or broken skin When using this product keep out of eyes. Rinse with waterto remove.
Stop use and ask a doctor if rash occurs

DOSAGE AND ADMINISTRATION

shake well before use .apply liberally and spread by hand 15 minutes before sun exposure .reapply:.after 80 minutes of swimming or sweating.immediatelyafter towel drying.at least every 2 hours

INDICATIONS AND USAGE

children under6 months of age:ask a doctor .Sun Protection Mleasures.Spending time in the sun increases your risk of skin cancerand early skin aging. To decrease this risk, reqularly usea sunscreen with a Broad Spectrum SPF value of 15 orhigher and other sun protection measures including:limittime in the sun, especially from 10 a.m.-2 p.m. .wear long-sleeved shirts, pants, hats, and sunglasses

INACTIVE INGREDIENT

Inactive ingredientswater,caprylic/capric triglyceride,dimethicone,tocopherol,glycerin, hydrogenated polyisobutene, butylene glycol dicaprylate/dicaprate,silica / silicon dioxide,vinyldimethicone/methicone silsesquioxane crosspolymer,triethoxycaprylylsilane,Osmanthus fragrans flower extract,trimethylsiloxysilicate, disteardimonium hectorite,butyleneglycol, Portulaca oleracea extract, Chrysanthellum indicum,Aloe barbadensis extract, Sophora angustifolia root extract.